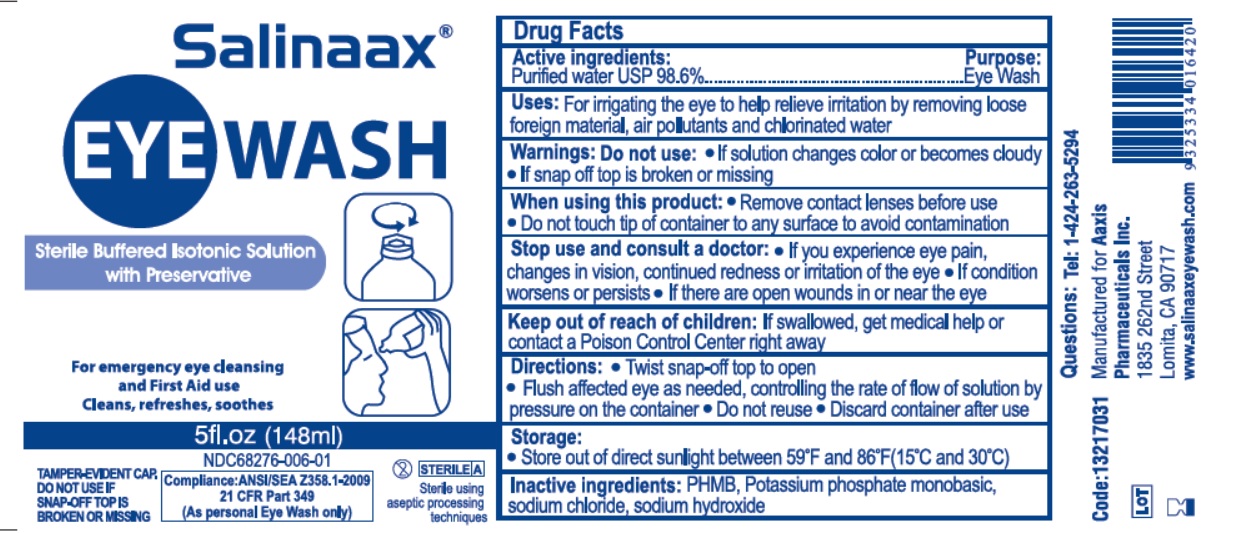 DRUG LABEL: Salinaax
NDC: 68276-006 | Form: RINSE
Manufacturer: Aaxis Pharmaceuticals Inc  Dba Aaxis Pacific
Category: otc | Type: HUMAN OTC DRUG LABEL
Date: 20180424

ACTIVE INGREDIENTS: Water 98.6 mL/100 mL
INACTIVE INGREDIENTS: Potassium phosphate, monobasic; Sodium chloride; Sodium hydroxide

Active Ingredient

Purified water USP 98.6%

Purpose

Eye Wash

Uses:

For irrigating the eye to help relieve irritation by removing loose foreign material, air pollutants, and chlorinated water.

Warnings

Do not use

- If solution changes color or becomes cloudy
- If snap off top is broken or missing

When using this product

- Remove contact lenses before use
- Do not touch the tip of container to any surface to acoid contamination

Stop use and consult a doctor

- If you experience eye pain, change in vision, continued redness or irritation of the eye
- If condition worsens or persists
- If there are open wounds in or near the eye

Keep out of reach of children

If swallowed, get medical help or contact a Poison Control Center right away.

Directions

- Twist snap-off top to open
- Flush affected eye as needed, controlling the rate of flow of solution by pressure on the container
- DO not reuse
- Discard container after use

Storage

Store out of direct sunlight between 59^0F and 86^0F (15^0C and 30^0C)

Inactive Ingredients:

PHMB,Potassium phosphate monobasic, sodium chloride USP, sodium hydroxide.

Questions

Tel: 1-424-263-5294

Principal Display Panel

NDC numbers - 68276-006-01, 02, 03, 04, 05

Salinaax

EYE WASH
Sterile Buffered Isotonic Solution with Preservative
For emergency eye cleaning and First Aid use.

Cleans, refreshes, soothes

TAMPER-EVIDENT CAP
DO NOT USE IF SNAP-OFF TOP IS BROKEN OR MISSING

STERILEA

Sterile using aseptic processing technique

68786-006-05.......... 0.5 fl.oz (15mL)

68786-006-01.......... 5.0 fl.oz (148mL)

68786-006-02.......... 8.0 fl.oz (236mL)

68786-006-03.......... 16 fl.oz (472mL)

68786-006-04.......... 32 fl.oz (944mL)